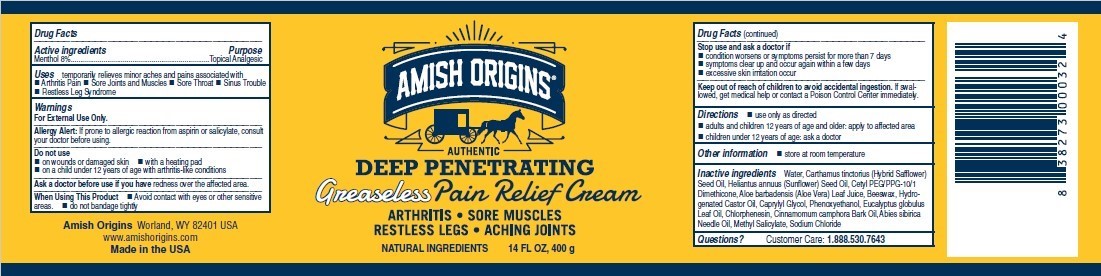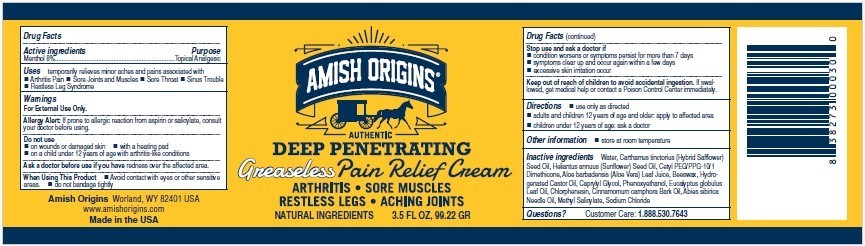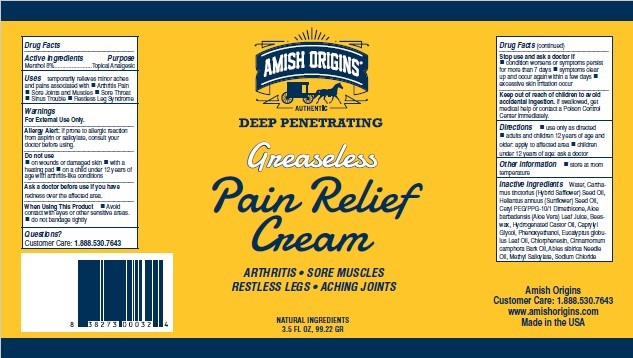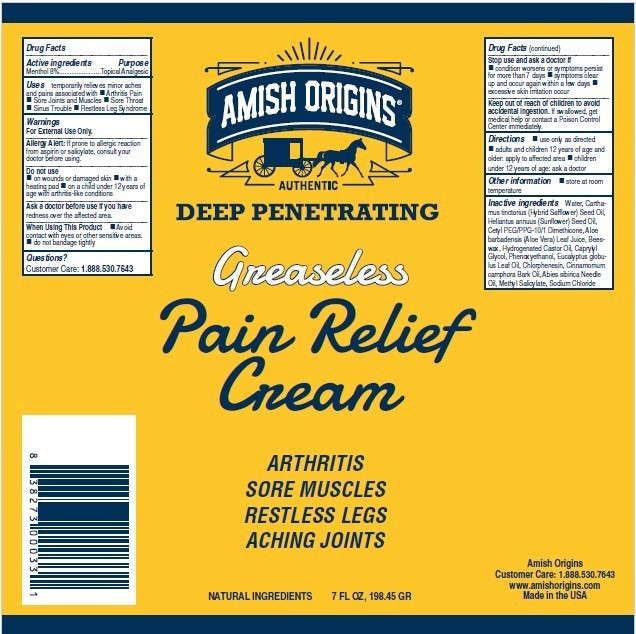 DRUG LABEL: Menthol
NDC: 62212-252 | Form: CREAM
Manufacturer: Amish Origins LLC
Category: otc | Type: HUMAN OTC DRUG LABEL
Date: 20241203

ACTIVE INGREDIENTS: MENTHOL 8 g/100 g
INACTIVE INGREDIENTS: WATER; SAFFLOWER OIL; SUNFLOWER SEED OIL GLYCERETH-8 ESTERS; CETYL PEG/PPG-10/1 DIMETHICONE (HLB 2); SODIUM CHLORIDE; ALOE VERA LEAF; HYDROGENATED CASTOR OIL; PHENOXYETHANOL; CAPRYLYL GLYCOL; CHLORPHENESIN; EUCALYPTUS GLOBULUS LEAF; CINNAMOMUM CAMPHORA WHOLE; ABIES SIBIRICA LEAF OIL; METHYL SALICYLATE

Amish Origins Medicated Cream

Active Ingredient

Menthol 8%

Purpose

Topical Analgesic

Uses:

Arthritis Pain, Sore Joints and Muscles, Sore Throat, Sinus Trouble, Restless Leg Syndrome

Warnings

- For External Use Only, As Directed!
- Avoid contact with eyes or other sensitive areas.
- If prone to allergic reaction from asprin or salicylate, consult your doctor before using.
- If conditions persist pore than seven days, consult your doctor
- If pregnant or breast-feeding, ask a health professional before use.
- Do not bandange tightly or use a heating pad
- May irritate sensitive skin

- Keep ointment out of reach of children

Directions

Adults and children over 12 years:

- Apply freely to affected areas. Rub well
- Colds: Apply on chest, back and neck.
- Head Colds: Apply around nostrils, on forehead and behind ears. Place small amount in vaporizer for aid.
- Sore Throat: Apply liberally on throat and neck for sore throats

Children 12 years or younger.

- Consult your physician.

INACTIVE INGREDIENTS

Water, Carthamus Tinctorius (Hybrid Safflower) Seed Oil, Cetyl PEG/PPG-10/1 Dimethicone, Aloe Barbadensis (Aleo Vera) Leaf Juice, Beeswax, Hydrogenated Castor oil, Caprylyl Glycol, Phenoxyethanol, Eucalyptus Globulus Leaf Oil, Chlorphenesin, Cinnamomum Camphora Bark Oil, Abies Sibirica Needle Oil, Methyl Salicylate, Sodium Chloride